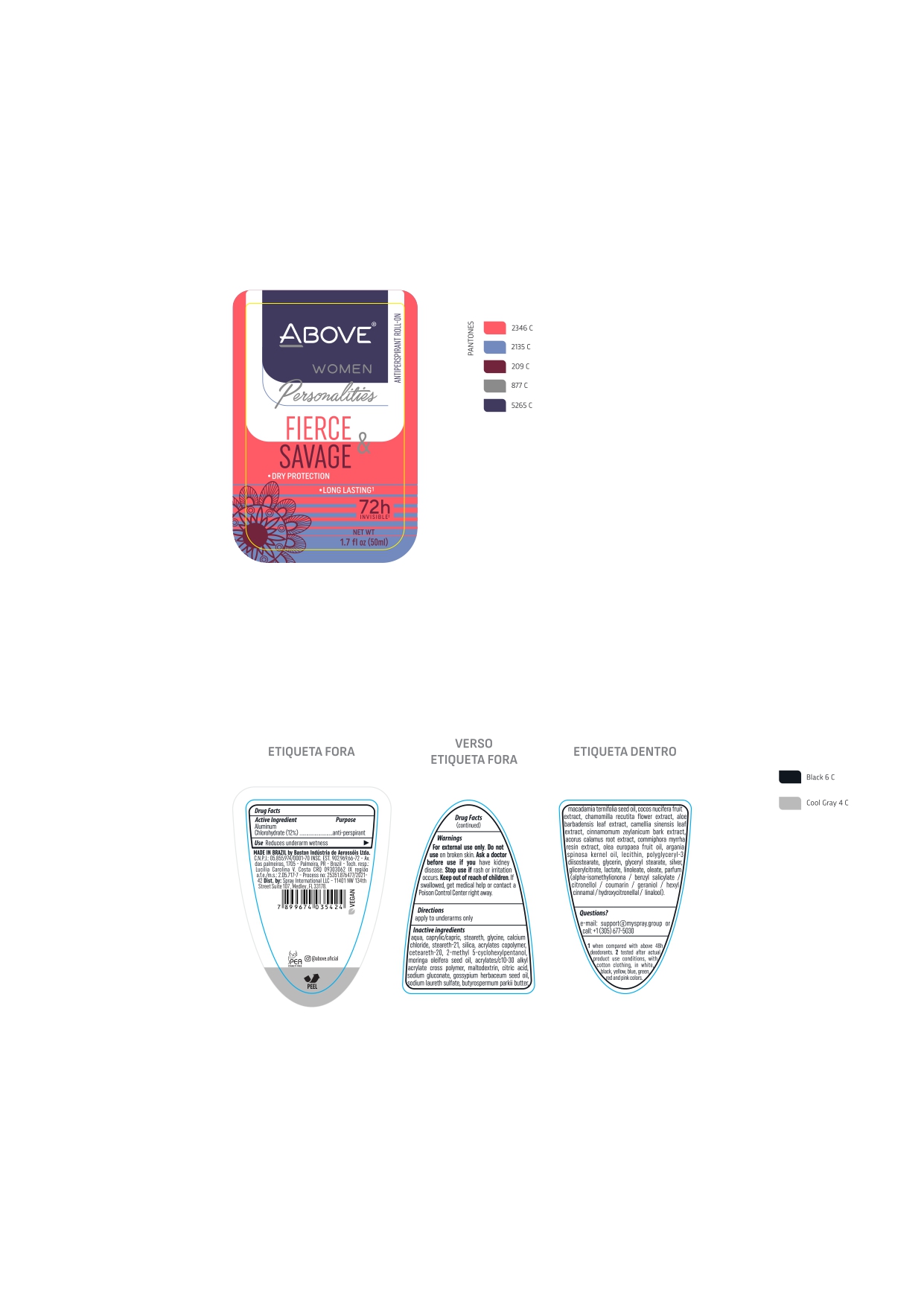 DRUG LABEL: ABOVE WOMEN PERSONALITIES FIERCE AND SAVAGE
NDC: 73306-1131 | Form: CREAM
Manufacturer: BASTON INDUSTRIA DE AEROSSOIS LTDA
Category: otc | Type: HUMAN OTC DRUG LABEL
Date: 20221114

ACTIVE INGREDIENTS: ALUMINUM CHLOROHYDRATE 12 mg/100 g
INACTIVE INGREDIENTS: MEDIUM-CHAIN TRIGLYCERIDES

ABOVE WOMEN PERSONALITIES FIERCE & SAVAGE